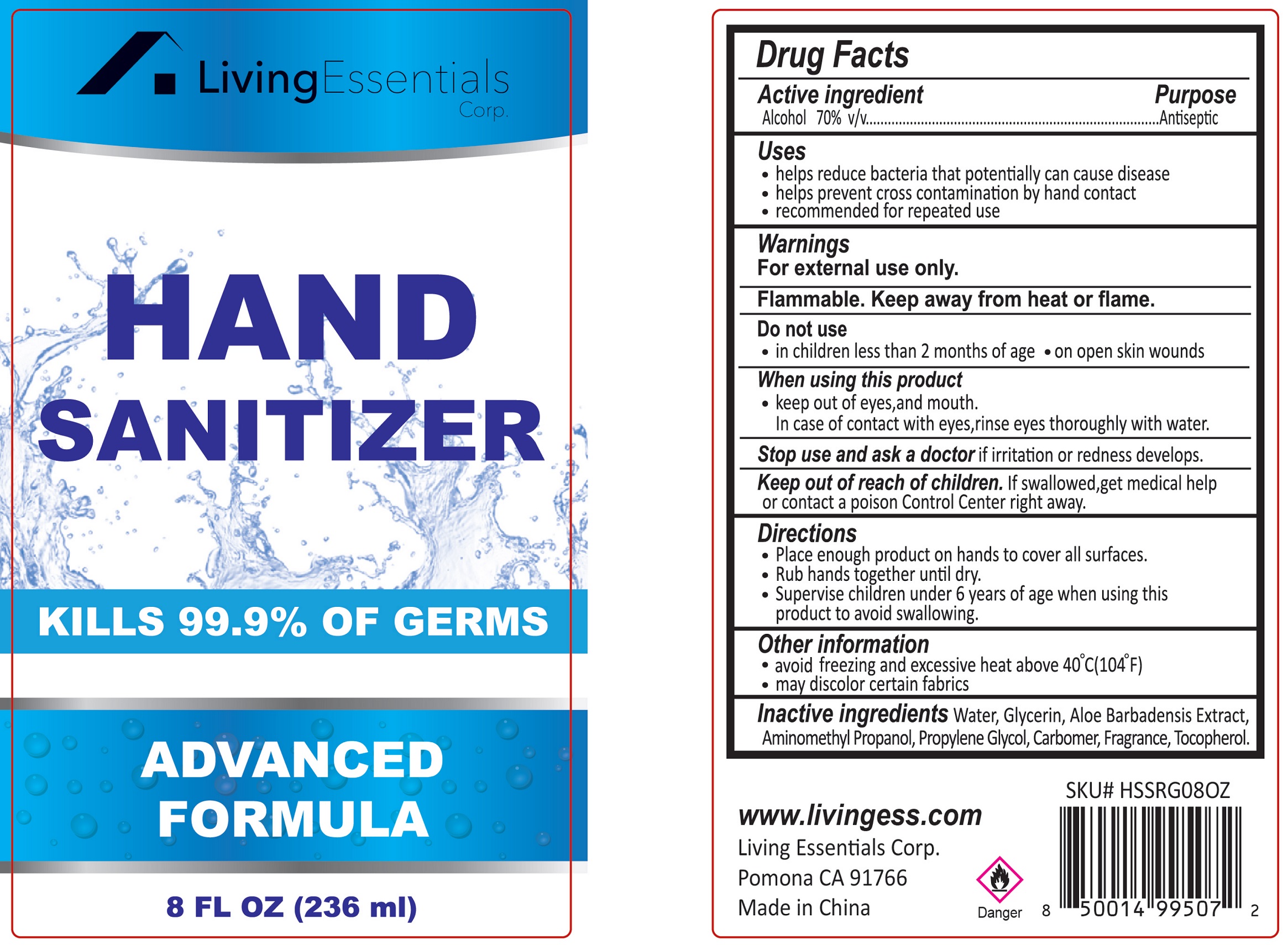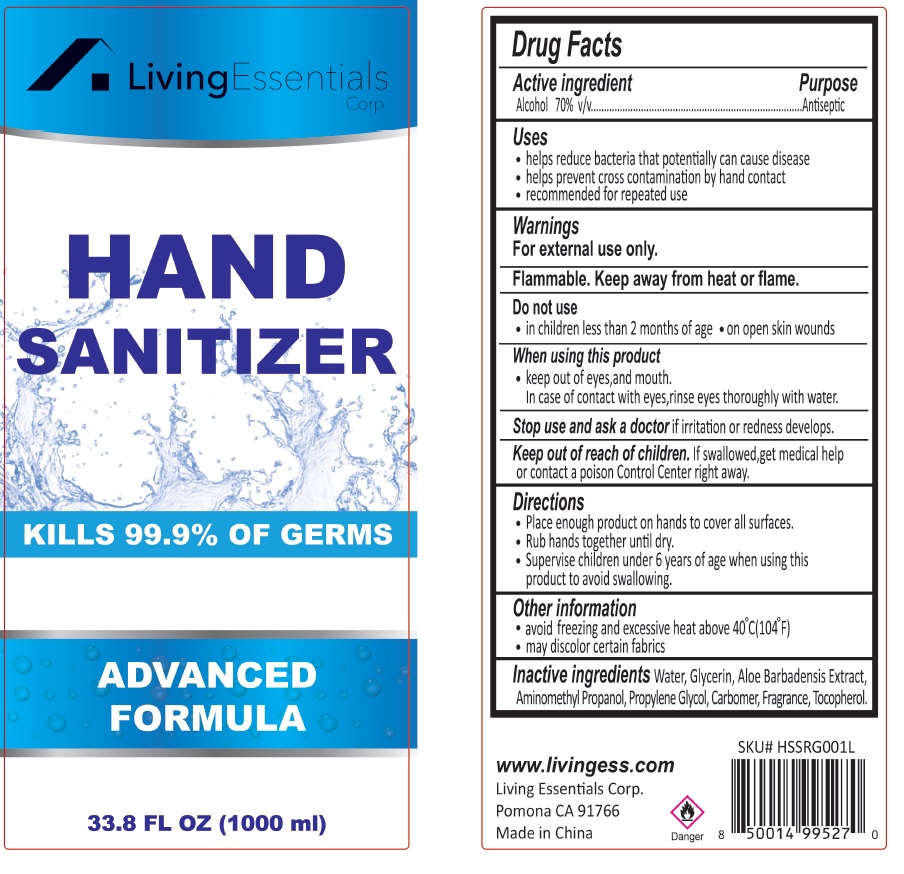 DRUG LABEL: Hand Sanitizer
NDC: 78628-008 | Form: GEL
Manufacturer: Living Essentials Corp.
Category: otc | Type: HUMAN OTC DRUG LABEL
Date: 20200608

ACTIVE INGREDIENTS: ALCOHOL 0.7 mL/1 mL
INACTIVE INGREDIENTS: WATER; GLYCERIN; ALOE VERA LEAF; AMINOMETHYLPROPANOL; PROPYLENE GLYCOL; CARBOMER HOMOPOLYMER, UNSPECIFIED TYPE; FRAGRANCE LAVENDER & CHIA F-153480; .ALPHA.-TOCOPHEROL ACETATE, D-

Hand Sanitizer

Active ingredient

Alcohol 70% v/v

Purpose

Antiseptic

Uses

- helps reduce bacteria that potentially can cause disease
- helps prevent coss contamination by hand contact
- recommended for repeated use

Warnings

For external use only.

Flammable. Keep away from heat or flame.

Do not use

- in children less than 2 months of age
- on open skin wounds

When using this product

- keep out of eyes, and mouth

In case of contact with eyes, rinse eyes thoroughly with water.

Stop use and ask a doctor

if irritation or redness develops.

Keep out of reach of children.

If swallowed,get medical help or contact a poison Control Center right away.

Directions

- Place enough product on hands to cover all surfaces.
- Rub hands together until dry.
- Supervise children under 6 years of age when using this product to avoid swallowing.

Other information

- avoid freezing and excessive heat above 40°C(104°F)
- may discolor certain fabrics

Inactive ingredients

Water, Glycerin, Aloe Barbadensis Extract, Aminomethyl Propanol, Propylene Glycol, Carbomer, Fragrance, Tocopherol.